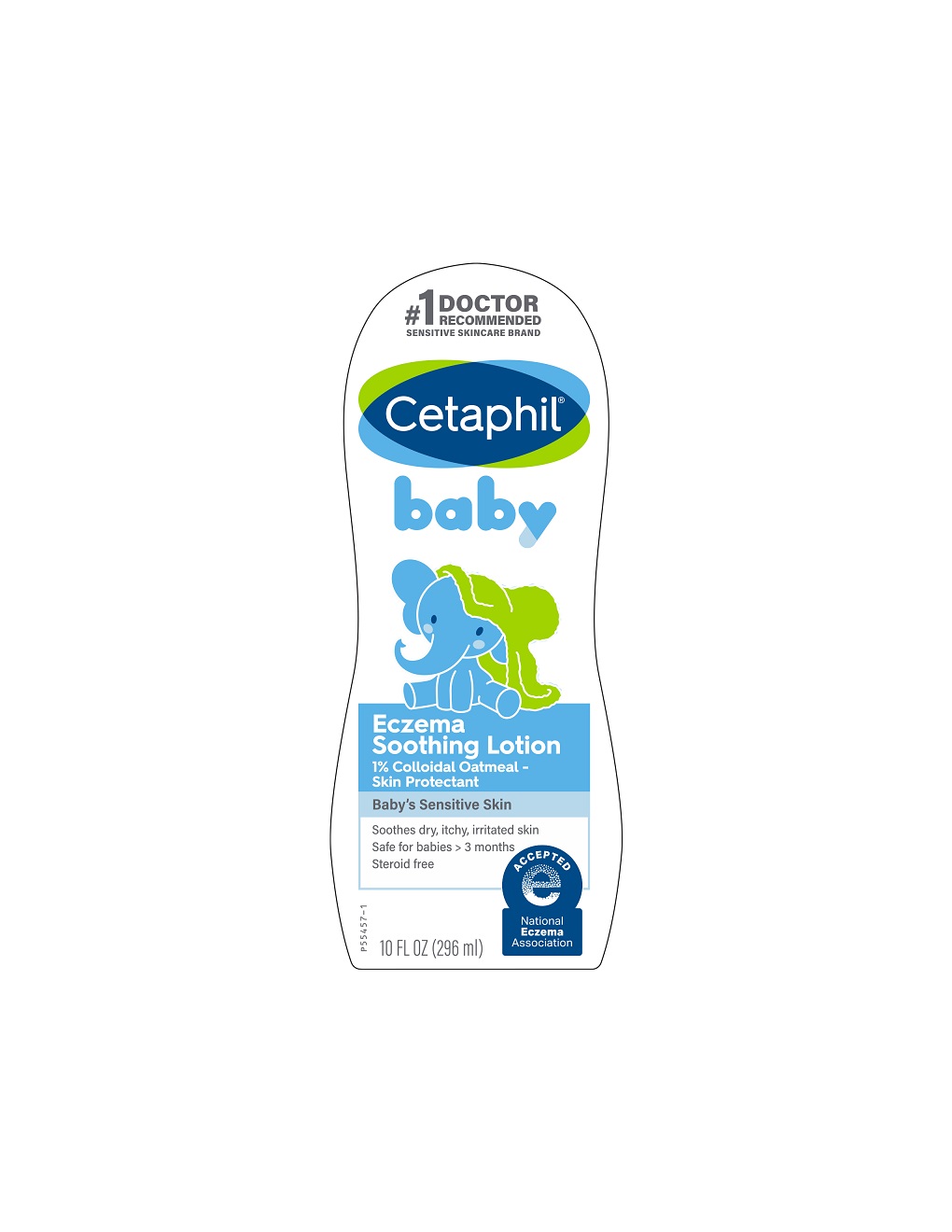 DRUG LABEL: Cetaphil Baby Eczema Soothing
NDC: 0299-4140 | Form: LOTION
Manufacturer: Galderma Laboratories, L.P.
Category: otc | Type: HUMAN OTC DRUG LABEL
Date: 20231122

ACTIVE INGREDIENTS: Oatmeal 1 g/100 mL
INACTIVE INGREDIENTS: Allantoin; Arginine; Docosanol; Shea Butter; Medium-chain Triglycerides; Caprylyl Glycol; Ceramide 3; Polyoxyl 20 Cetostearyl Ether; Cetostearyl Alcohol; Cetyl Alcohol; Citric Acid Monohydrate; Cyclomethicone 5; Dimethiconol (100000 Cst); Edetate Disodium; Disodium Ethylene Dicocamide Peg-15 Disulfate; Glycerin; Glyceryl Monostearate; Glyceryl Stearate Citrate; Sunflower Oil; Niacinamide; Panthenol; Pentylene Glycol; Hyaluronate Sodium; Sodium Pyrrolidone Carboxylate; Sodium Polyacrylate (2500000 Mw); Sorbitol; .alpha.-tocopherol Acetate; Water

Drug Facts

Active ingredients......Purpose

Colloidal Oatmeal 1%......Skin Protectant

Uses

Temporarily protects and helps relieve minor skin irritation and itching due to:
●Eczema ●Rashes

Warnings

For external use only.

When using this product ● Do not get into eyes.

Stop use and ask a Doctor if ● condition worsens ● symptoms last more than 7 days or clear up and occur again within a few days.

Keep out of reach of children. If swallowed, get medical help or contact a Poison Control Center right away.

Directions

Apply as needed

Inactive Ingredients

Allantoin, Arginine, Behenyl Alcohol, Butyrospermum Parkii, (Shea) Butter, Caprylic/Capric Triglyceride, Caprylyl Glycol, Ceramide NP, Ceteareth-20, Cetearyl Alcohol, Cetyl Alcohol, Citric Acid, Cyclopentasiloxane, Dimethiconol, Disodium EDTA, Disodium Ethylene Dicocamide PEG-15 Disulfate, Glycerin, Glyceryl Stearate, Glyceryl Stearate Citrate, Helianthus Annuus (Sunflower) Seed Oil, Niacinamide, Panthenol, Pentylene Glycol, Sodium Hyaluronate, Sodium PCA, Sodium Polyacrylate, Sorbitol, Tocopheryl Acetate, Water

Questions or comments?

1-866-735-4137

Distributed By:
Galderma Laboratories, L.P.
Fort Worth, TX 76177

All trademarks are the property of their respective owners

Made in Canada

Cetaphil.com

PRINCIPLE DISPLAY PANEL - 10 oz bottle

#1 Doctor Recommended
Sensitive Skincare Brand
Cetaphil®

baby

Eczema
Soothing Lotion

1% Colloidal Oatmeal -

Skin Protectant

Baby's Sensitive skin

Soothes dry, itchy, irritated skin
Safe for babies > 3 months
Steroid free

NATIONAL
ECZEMA
ASSOCIATION LOGO

10 FL OZ (296 ml)
P55457-1